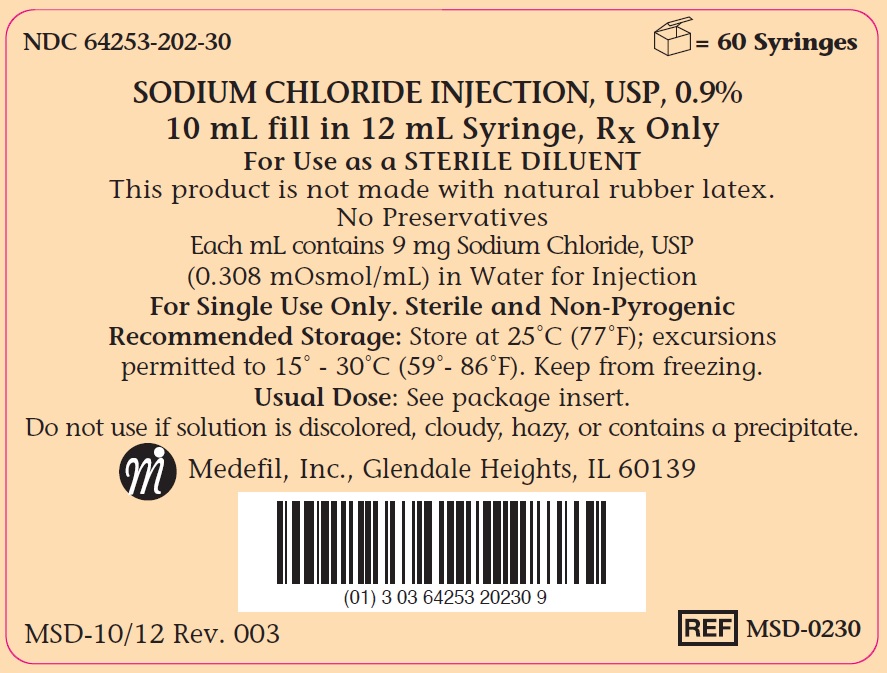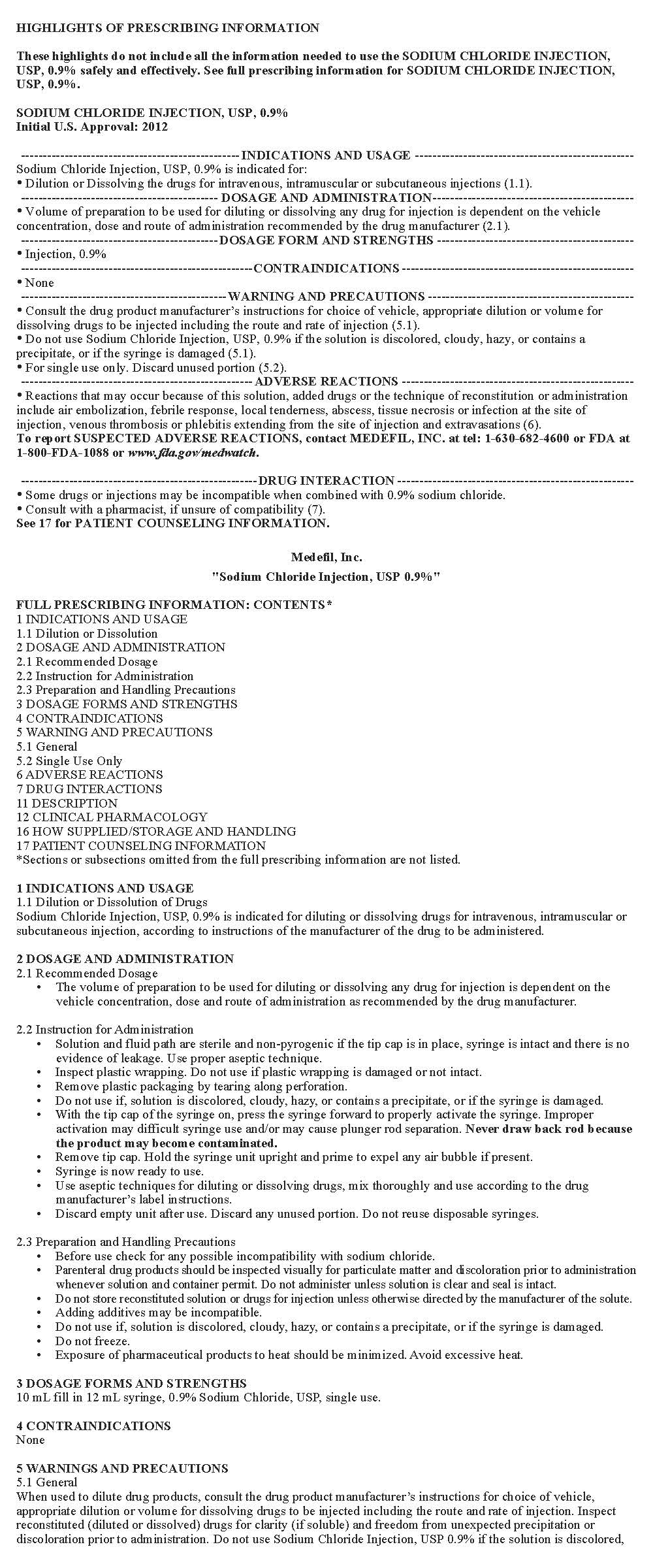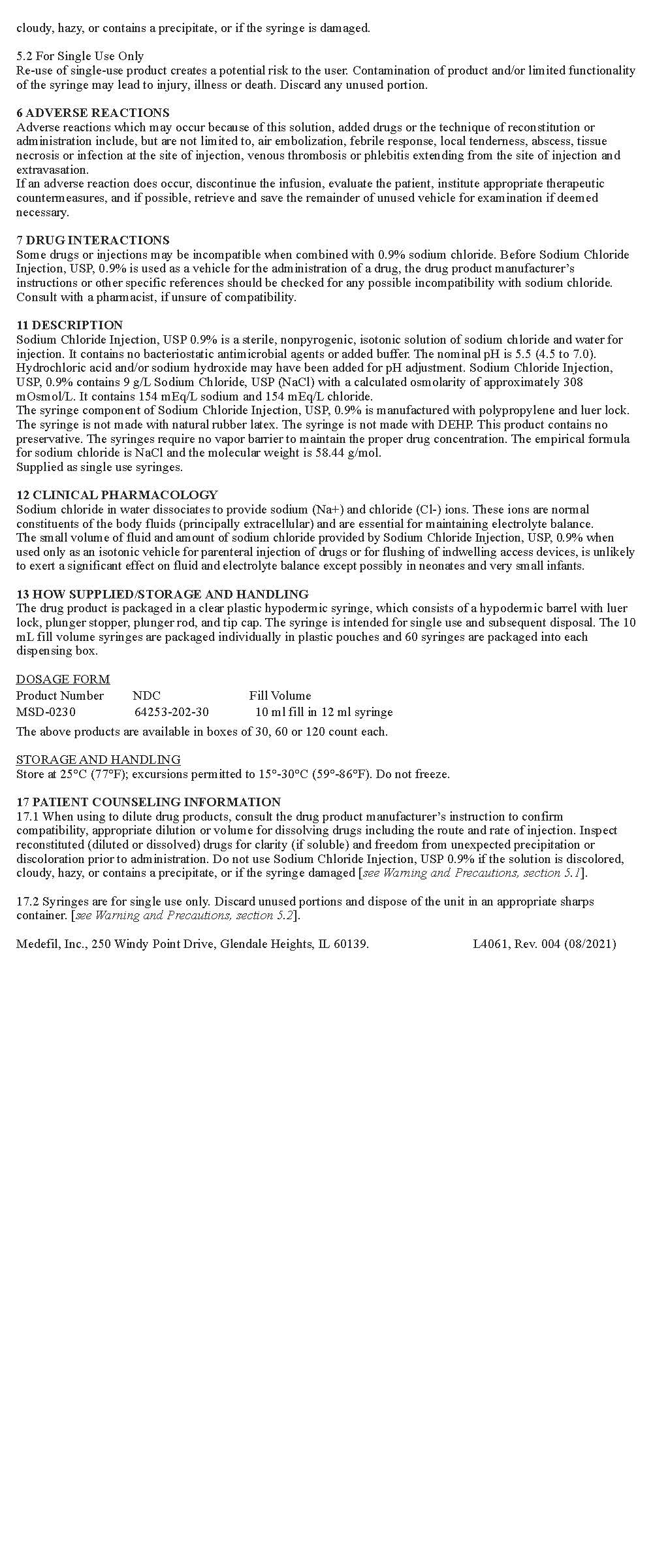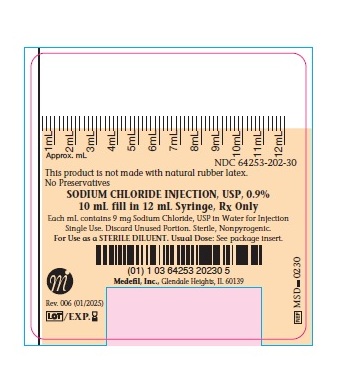 DRUG LABEL: sodium chloride
NDC: 64253-202 | Form: INJECTION, SOLUTION
Manufacturer: Medefil, Inc.
Category: prescription | Type: HUMAN PRESCRIPTION DRUG LABEL
Date: 20260226

ACTIVE INGREDIENTS: SODIUM CHLORIDE 9 mg/1 mL
INACTIVE INGREDIENTS: WATER

HIGHLIGHTS OF PRESCRIBING INFORMATION

These highlights do not include all the information needed to use SODIUM CHLORIDE INJECTION, USP, 0.9% safely and effectively. See full prescribing information for SODIUM CHLORIDE INJECTION, USP, 0.9%.
SODIUM CHLORIDE INJECTION, USP, 0.9%
Initial U.S. Approval: 2012

1 INDICATIONS & USAGE

Sodium Chloride Injection, USP, 0.9% is indicated for:

• Dilution or Dissolving the drugs for intravenous, intramuscular or subcutaneous injections (1.1).

2 DOSAGE & ADMINISTRATION

• Volume of preparation to be used for diluting or dissolving any drug for injection is dependent on the vehicle concentration, dose and route of administration recommended by the drug manufacturer (2.1).

3 DOSAGE FORMS & STRENGTHS

• Injection, 0.9%

4 CONTRAINDICATIONS

• None

5 WARNINGS AND PRECAUTIONS

• Consult the drug product manufacturer’s instructions for choice of vehicle, appropriate dilution or volume for dissolving drugs to be injected including the route and rate of injection (5.1).

• Do not use Sodium Chloride Injection, USP, 0.9% if the solution is discolored, cloudy, hazy, or contains a precipitate, or if the syringe is damaged (5.1).

• For single use only. Discard unused portion (5.2).

6 ADVERSE REACTIONS

• Reactions that may occur because of this solution, added drugs or the technique of reconstitution or administration include air embolization, febrile response, local tenderness, abscess, tissue necrosis or infection at the site of injection, venous thrombosis or phlebitis extending from the site of injection and extravasations (6).

To report SUSPECTED ADVERSE REACTIONS, contact MEDEFIL, INC. at tel:1-630-682-4600 and http://www.medefilinc.com/ or FDA at 1-800-FDA-1088 or www.fda.gov/medwatch.

7 DRUG INTERACTIONS

• Some drugs or injections may be incompatible when combined with 0.9% sodium chloride.

• Consult with a pharmacist, if unsure of compatibility (7).

FULL PRESCRIBING INFORMATION

1 INDICATIONS & USAGE

1.1 Dilution or Dissolution of Drugs

Sodium Chloride Injection, USP, 0.9% is indicated for diluting or dissolving drugs for intravenous, intramuscular or subcutaneous injection, according to instructions of the manufacturer of the drug to be administered.

2 DOSAGE & ADMINISTRATION

2.1 Recommended Dosage

- The volume of preparation to be used for diluting or dissolving any drug for injection is dependent on the vehicle concentration, dose and route of administration as recommended by the drug manufacturer.

2.2 Instruction for Administration

- Solution and fluid path are sterile and non-pyrogenic if the tip cap is in place, syringe is intact and there is no evidence of leakage. Use proper aseptic technique.
- Inspect plastic wrapping. Do not use if plastic wrapping is damaged or not intact. (Figure 1)
- Remove plastic packaging by tearing along perforation. (Figure 2)
- Do not use if, solution is discolored, cloudy, hazy, or contains a precipitate, or if the syringe is damaged. (Figure 3)
- With the tip cap of the syringe on, press the syringe forward to properly activate the syringe. Improper activation may difficult syringe use and/or may cause plunger rod separation. Never draw back rod because the product may become contaminated. (Figure 4)
- Remove tip cap. Hold the syringe unit upright and prime to expel any air bubble if present. (Figure 5)
- Syringe is now ready to use.
- Use aseptic techniques for diluting or dissolving drugs, mix thoroughly and use according to the drug manufacturer’s label instructions.
- Discard empty unit after use. Discard any unused portion. Do not reuse disposable syringes.

2.3 Preparation and Handling Precautions

- Before use check for any possible incompatibility with sodium chloride.
- Parenteral drug products should be inspected visually for particulate matter and discoloration prior to administration whenever solution and container permit. Do not administer unless solution is clear and seal is intact.
- Do not store reconstituted solution or drugs for injection unless otherwise directed by the manufacturer of the solute.
- Adding additives may be incompatible.
- Do not use if, solution is discolored, cloudy, hazy, or contains a precipitate, or if the syringe is damaged.
- Do not freeze.
- Exposure of pharmaceutical products to heat should be minimized. Avoid excessive heat.

3 DOSAGE FORMS & STRENGTHS

10 mL fill in 12 mL syringe, 0.9% Sodium Chloride, USP, single use.

4 CONTRAINDICATIONS

None

5 WARNINGS AND PRECAUTIONS

5.1 General

When used to dilute drug products, consult the drug product manufacturer’s instructions for choice of vehicle, appropriate dilution or volume for dissolving drugs to be injected including the route and rate of injection. Inspect reconstituted (diluted or dissolved) drugs for clarity (if soluble) and freedom from unexpected precipitation or discoloration prior to administration. Do not use Sodium Chloride Injection, USP 0.9% if the solution is discolored, cloudy, hazy, or contains a precipitate, or if the syringe is damaged.

5.2 For Single Use Only

Re-use of single-use product creates a potential risk to the user. Contamination of product and/or limited functionality of the syringe may lead to injury, illness or death. Discard any unused portion.

6 ADVERSE REACTIONS

Adverse reactions which may occur because of this solution, added drugs or the technique of reconstitution or administration include, but are not limited to, air embolization, febrile response, local tenderness, abscess, tissue necrosis or infection at the site of injection, venous thrombosis or phlebitis extending from the site of injection and extravasation.

If an adverse reaction does occur, discontinue the infusion, evaluate the patient, institute appropriate therapeutic countermeasures, and if possible, retrieve and save the remainder of unused vehicle for examination if deemed necessary.

7 DRUG INTERACTIONS

Some drugs or injections may be incompatible when combined with 0.9% sodium chloride. Before Sodium Chloride Injection, USP, 0.9% is used as a vehicle for the administration of a drug, the drug product manufacturer’s instructions or other specific references should be checked for any possible incompatibility with sodium chloride.

Consult with a pharmacist, if unsure of compatibility.

11 DESCRIPTION

Sodium Chloride Injection, USP 0.9% is a sterile, nonpyrogenic, isotonic solution of sodium chloride and water for injection. It contains no bacteriostatic antimicrobial agents or added buffer. The nominal pH is 5.5 (4.5 to 7.0).

Hydrochloric acid and/or sodium hydroxide may have been added for pH adjustment. Sodium Chloride Injection, USP, 0.9% contains 9 g/L Sodium Chloride, USP (NaCl) with a calculated osmolarity of approximately 308 mOsmol/L. It contains 154 mEq/L sodium and 154 mEq/L chloride.

The syringe component of Sodium Chloride Injection, USP, 0.9% is manufactured with polypropylene and luer lock.

The syringe is not made with natural rubber latex. The syringe is not made with DEHP. This product contains no preservative. The syringes require no vapor barrier to maintain the proper drug concentration. The empirical formula for sodium chloride is NaCl and the molecular weight is 58.44 g/mol.

Supplied as single use syringes.

12 CLINICAL PHARMACOLOGY

Sodium chloride in water dissociates to provide sodium (Na+) and chloride (Cl-) ions. These ions are normal constituents of the body fluids (principally extracellular) and are essential for maintaining electrolyte balance.

The small volume of fluid and amount of sodium chloride provided by Sodium Chloride Injection, USP, 0.9% when used only as an isotonic vehicle for parenteral injection of drugs or for flushing of indwelling access devices, is unlikely to exert a significant effect on fluid and electrolyte balance except possibly in neonates and very small infants.

16 HOW SUPPLIED/STORAGE AND HANDLING

The drug product is packaged in a clear plastic hypodermic syringe, which consists of a hypodermic barrel with luer lock, plunger stopper, plunger rod, and tip cap. The syringe is intended for single use and subsequent disposal. The 10 mL fill volume syringes are packaged individually in plastic pouches and 60 syringes are packaged into each dispensing box.

DOSAGE FORM

Product Number | NDC | Fill Volume
MSD-0230 | 64253-202-30 | 10 mL fill in 12 mL syringe

The above product is available in boxes of 30, 60 or 120 count each.

STORAGE AND HANDLING

Store at 25°C (77°F); excursions permitted to 15°-30°C (59° - 86°F). Do not freeze.

17 PATIENT COUNSELING INFORMATION

17.1 When using to dilute drug products, consult the drug product manufacturer’s instruction to confirm compatibility, appropriate dilution or volume for dissolving drugs including the route and rate of injection. Inspect reconstituted (diluted or dissolved) drugs for clarity (if soluble) and freedom from unexpected precipitation or discoloration prior to administration. Do not use Sodium Chloride Injection, USP 0.9% if the solution is discolored, cloudy, hazy, or contains a precipitate, or if the syringe damaged [ see Warning and Precautions, section 5.1].

17.2 Syringes are for single use only. Discard unused portions and dispose of the unit in an appropriate sharps container. [ see Warning and Precaustions, section 5.2].

Medefil, Inc., 250 Windy Point Drive, Glendale Heights, IL 60139. Prepared 10/2020 Rev. 003

PACKAGE LABEL.PRINCIPAL DISPLAY PANEL

Manufactured by:

Medefil, Inc., 250 Windy Point Drive, Glendale Heights, IL 60139.

NDA 202832

Rev. 003

Package Insert_Page 1 and 2